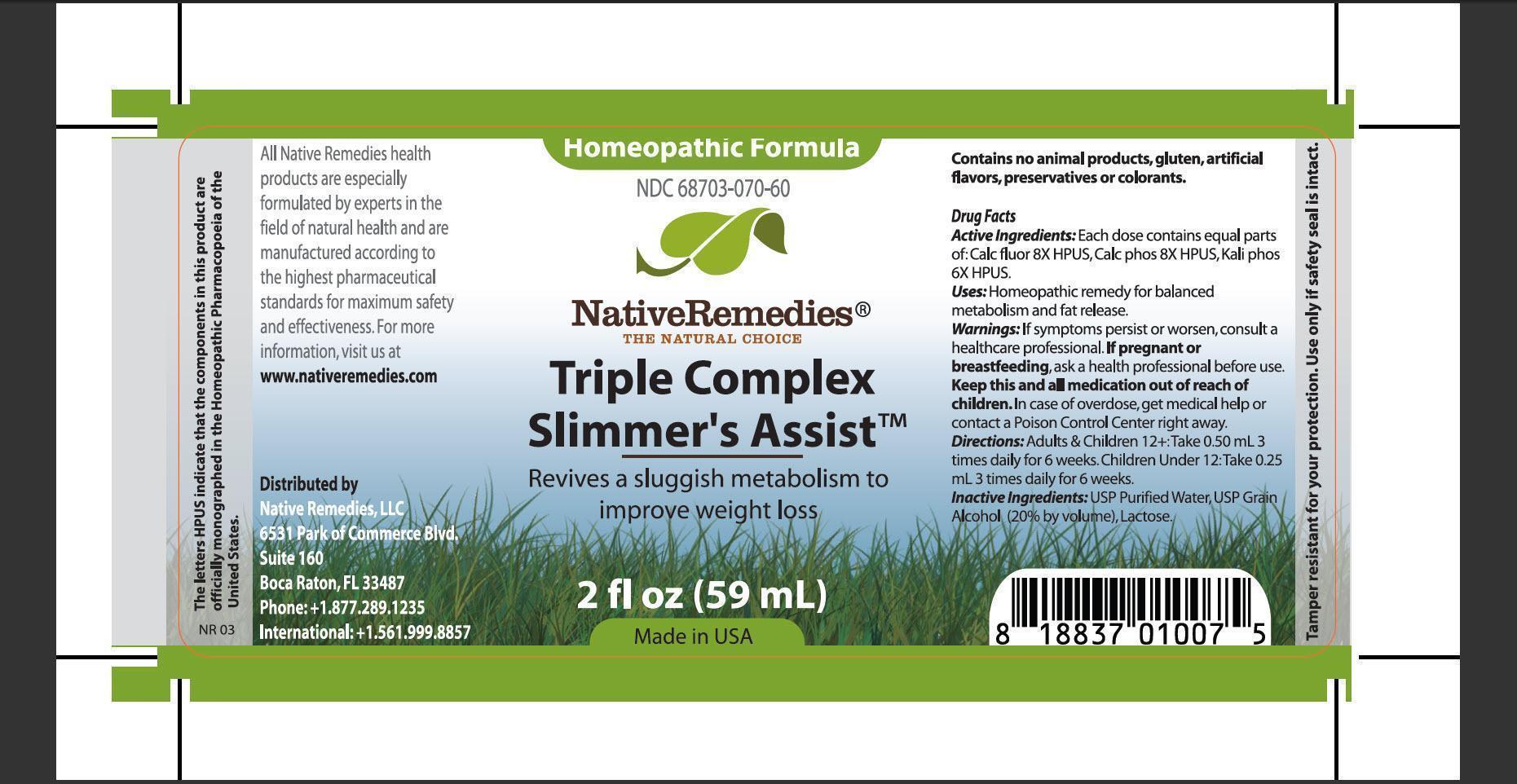 DRUG LABEL: TripleComplex Slimmers Assist
NDC: 68703-070 | Form: TINCTURE
Manufacturer: Native Remedies, LLC
Category: homeopathic | Type: HUMAN OTC DRUG LABEL
Date: 20130404

ACTIVE INGREDIENTS: CALCIUM FLUORIDE 8 [hp_X]/1 mL; TRIBASIC CALCIUM PHOSPHATE 8 [hp_X]/1 mL; POTASSIUM PHOSPHATE, DIBASIC 8 [hp_X]/1 mL
INACTIVE INGREDIENTS: WATER; ALCOHOL; LACTOSE

Triple Complex Slimmers Assist

PURPOSE

Revives a sluggish metabolism to improve weight loss

ACTIVE INGREDIENT

Active Ingredients: Each dose contains equal parts of: Calc fluor 8X HPUS, Calc phos 8X HPUS, Kali phos 6X HPUS

INDICATIONS AND USAGE

Uses: Homeopathic remedy for balanced metabolism and fat release

WARNINGS

Warnings: If symptoms persist or worsen, consult a healthcare professional

PREGNANCY OR BREAST FEEDING

If pregnant or breastfeeding, ask a health professional before use

KEEP OUT OF REACH OF CHILDREN

Keep this and all medication out of reach of children

OVERDOSAGE

In case of overdose, get medical help or contact Poison Control Center right away

DOSAGE AND ADMINISTRATION

Directions: Adults and Children 12+: Take 0.50 mL 3 times daily for 6 weeks. Children Under 12: Take 0.25 mL 3 times daily for 6 weeks

INACTIVE INGREDIENT

Inactive Ingredients: USP Purified Water, USP Grain Alcohol (20% by volume), Lactose

PATIENT COUNSELING INFORMATION

The letters HPUS indicate that the components in this product are officially monographed in the Homeopathic Pharmacopoeia of the United States

All Native Remedies health products are especially formulated by experts in the field of natural health and are manufactured according to the highest pharmaceutical standards for maximum safety and effectiveness. For more information, visit us at www.nativeremedies.com

Distributed by
Native Remedies, LLC
6531 Park of Commerce Blvd.
Suite 160
Boca Raton, FL 33487
Phone: +1.877.289.1235
International: +1.561.999.8857

Contains no animal products, gluten, artificial flavors, preservatives or colorants

STORAGE AND HANDLING

Tamper resistant for your protection. Use only if safety seal is intact